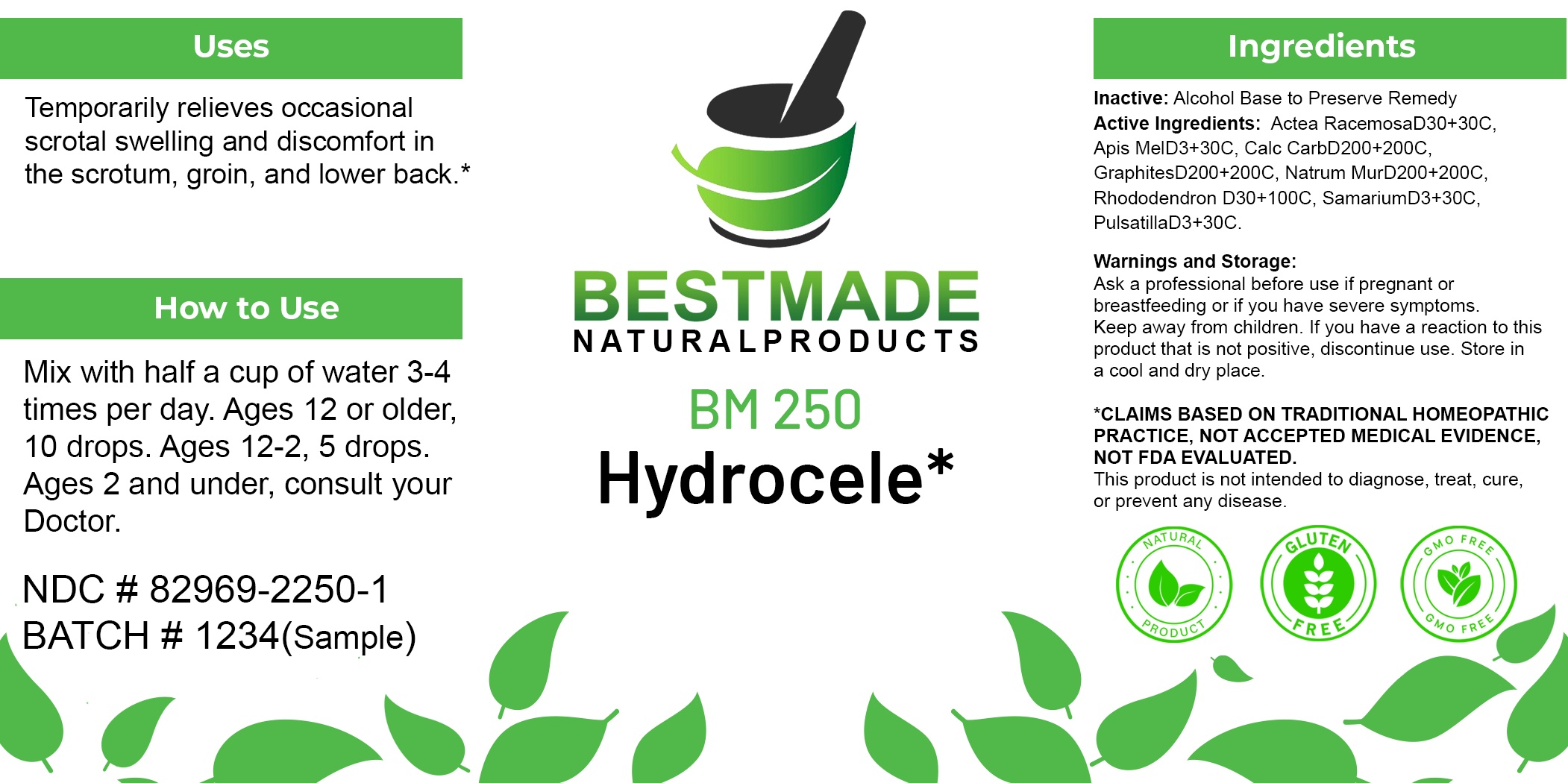 DRUG LABEL: Bestmade Natural Products BM250
NDC: 82969-2250 | Form: LIQUID
Manufacturer: Bestmade Natural Products
Category: homeopathic | Type: HUMAN OTC DRUG LABEL
Date: 20250327

ACTIVE INGREDIENTS: OYSTER SHELL CALCIUM CARBONATE, CRUDE 30 [hp_C]/30 [hp_C]; RHODODENDRON FERRUGINEUM FLOWER 30 [hp_C]/30 [hp_C]; SODIUM CHLORIDE 30 [hp_C]/30 [hp_C]; PULSATILLA PRATENSIS WHOLE 30 [hp_C]/30 [hp_C]; GRAPHITE 30 [hp_C]/30 [hp_C]; SAMARIUM 30 [hp_C]/30 [hp_C]; APIS MELLIFERA 30 [hp_C]/30 [hp_C]; ACTAEA RACEMOSA WHOLE 30 [hp_C]/30 [hp_C]
INACTIVE INGREDIENTS: ALCOHOL 30 [hp_C]/30 [hp_C]

BM250

DOSAGE AND ADMINISTRATION

How to Use
Mix with half a cup of water 3-4 times per day. Ages 12 or older, 10 drops. Ages 12-2, 5 drops. Ages 2 and under, consult your Doctor.

INDICATIONS AND USAGE

Use: Temporarily relieves occasional scrotal swelling and discomfort in the scrotum, groin, and lower back.*

INACTIVE INGREDIENT

Ingredients
Inactive: Alcohol Base to Preserve Remedy

ACTIVE INGREDIENT

Active Ingredients: Actea RacemosaD30+ 30C, Apis MelD3+30C, Calc CarbD200+200C, GraphitesD200+200C, Natrum MurD200+200C, RhododendronD30+100C, SamariumD3+30C, PulsatillaD3+30C

KEEP OUT OF REACH OF CHILDREN

Warnings and Storage:

Ask a professional before use if pregnant or breastfeeding or if you have severe symptoms.
Keep away from children.
If you have a reaction to this product that is not positive, discontinue use.
Store in a cool and dry place.
*CLAIMS BASED ON TRADITIONAL HOMEOPATHIC PRACTICE, NOT ACCEPTED MEDICAL EVIDENCE, NOT FDA EVALUATED.
This product is not intended to diagnose, treat, cure, or prevent any disease.

PURPOSE

Use: Temporarily relieves occasional scrotal swelling and discomfort in the scrotum, groin, and lower back.*

Warnings and Storage:
Ask a professional before use if pregnant or breastfeeding or if you have severe symptoms.
Keep away from children.
If you have a reaction to this product that is not positive, discontinue use.
Store in a cool and dry place.
*CLAIMS BASED ON TRADITIONAL HOMEOPATHIC PRACTICE, NOT ACCEPTED MEDICAL EVIDENCE, NOT FDA EVALUATED.
This product is not intended to diagnose, treat, cure, or prevent any disease.

Entire package label